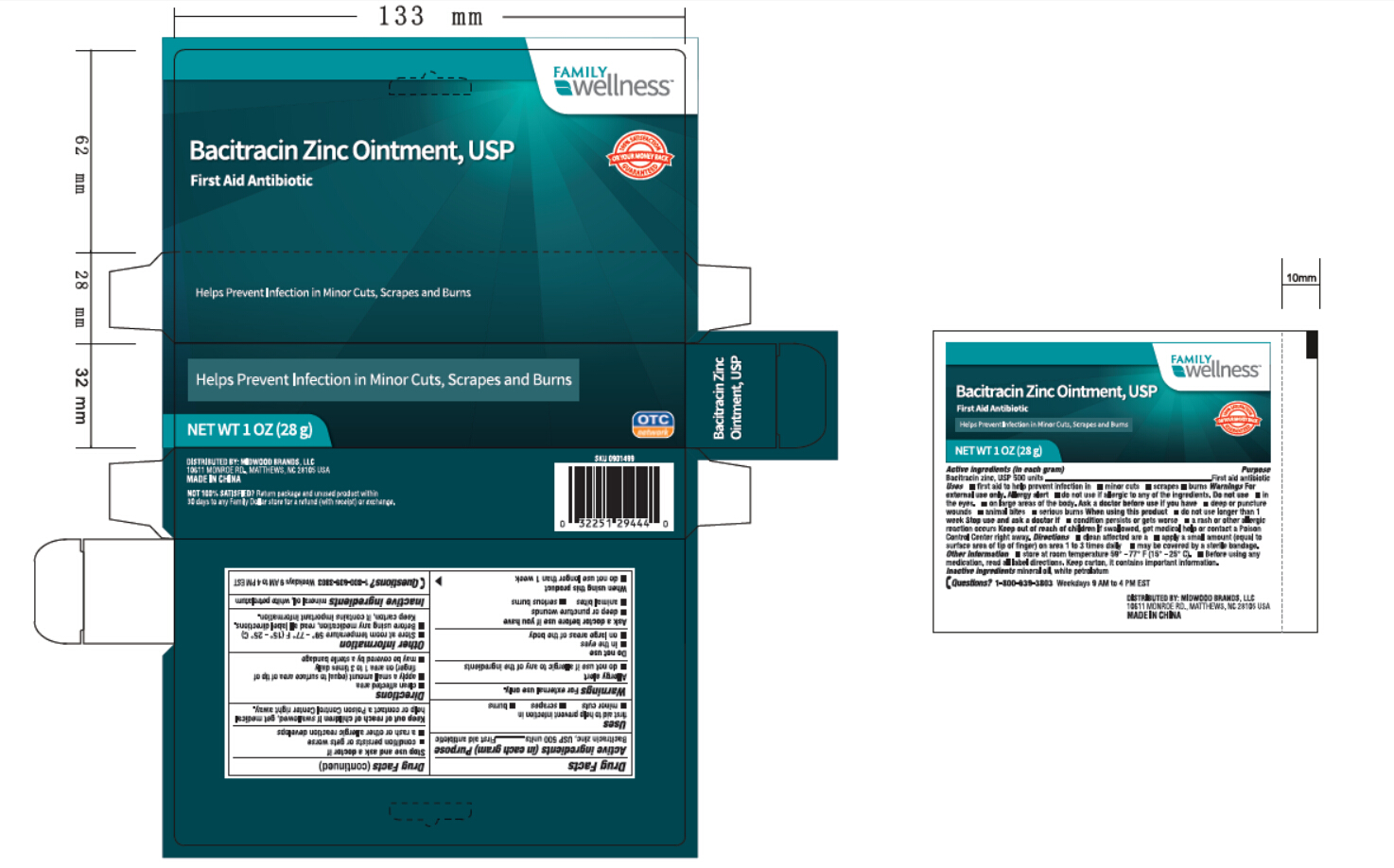 DRUG LABEL: Family Wellness
NDC: 69571-008 | Form: OINTMENT
Manufacturer: FRONT PHARMACEUTICAL PLC
Category: otc | Type: HUMAN OTC DRUG LABEL
Date: 20231027

ACTIVE INGREDIENTS: BACITRACIN ZINC 0.51 g/100 g
INACTIVE INGREDIENTS: MINERAL OIL; PETROLATUM

Active ingredients (in each gram)

Bacitracin zinc, USP 500 units

Purpose

First aid antibiotic

Uses

first aid to help prevent infection in

•minor cuts •scrapes •burns

Warnings For external use only

Allergy alert

•do not use if allergic to any of the ingredients

Do not use

•in or near eyes

•on large areas of the body

Ask a doctor before use if you have

•deep or puncture wounds

•animal bites •serious burns

When using this product

•do not use longer than 1 week

Stop use and ask a doctor if

•condtions last or gets worse

•symptoms last for more than 7 days or clear up and

come back within a few days

•if rash or other allergic reaction occurs

KEEP OUT OF REACH OF CHILDREN

If swallowed, get medical Keep out of reach of children.

help or contact a Poison Control Center right away.

Directions

•adults and children 2 years of age and older:

•clean affected area

•apply a small amount (equal to surface area of tip of

finger) on area 1 to 3 times dailt

•may be covered by a sterile bandage

•children under 2 years of age:

•ask a doctor

Other Information

•Store at room temperature 54° - 77° (15° - 25° C)

•Before using any medication, read all label direcitons.

Keep carton. It contains important information

mineral oil, white petrolatum Inactive ingredients

QUESTIONS

1-800-639-3803 Weekdays 9 AM to 4 PM EST Questions?